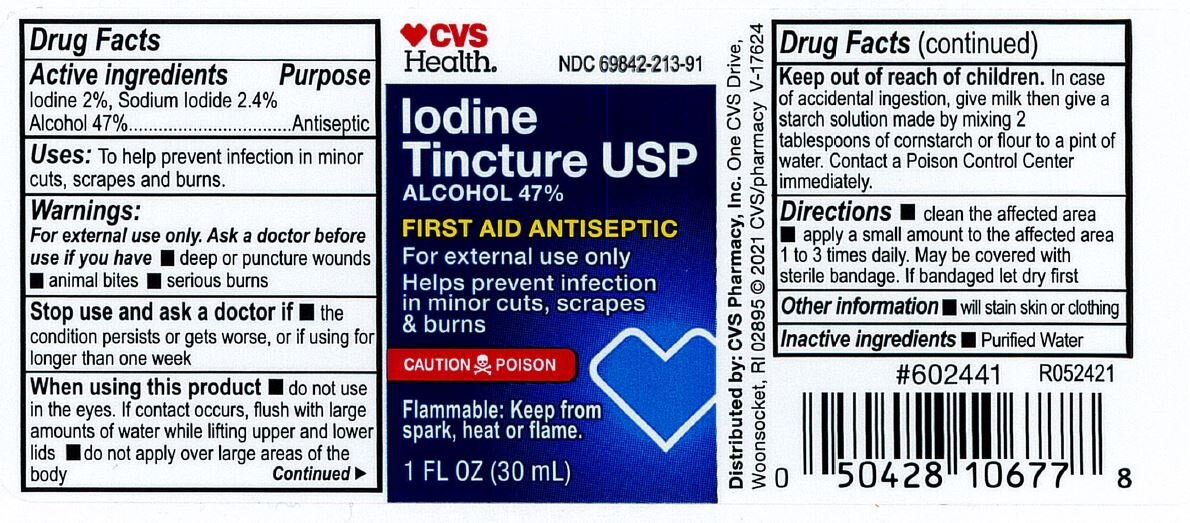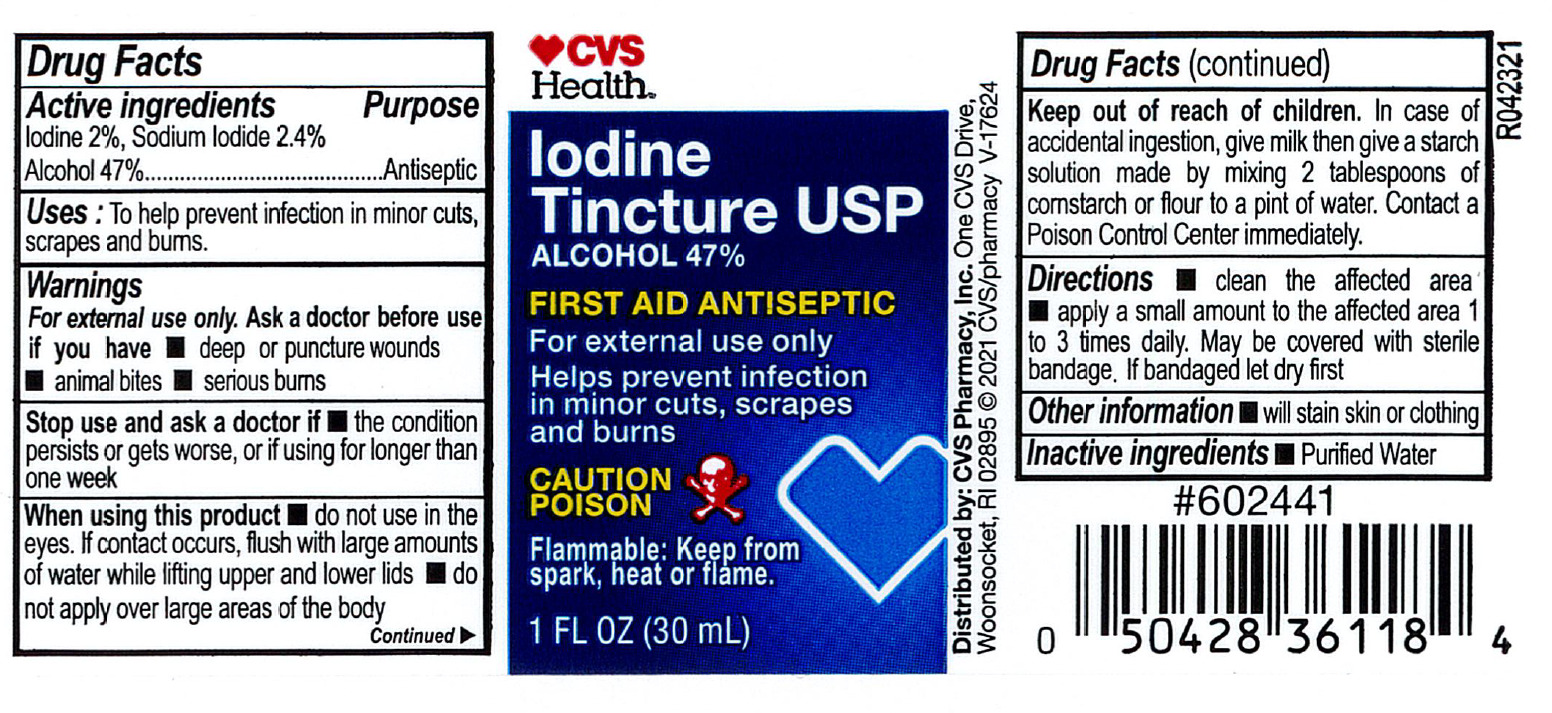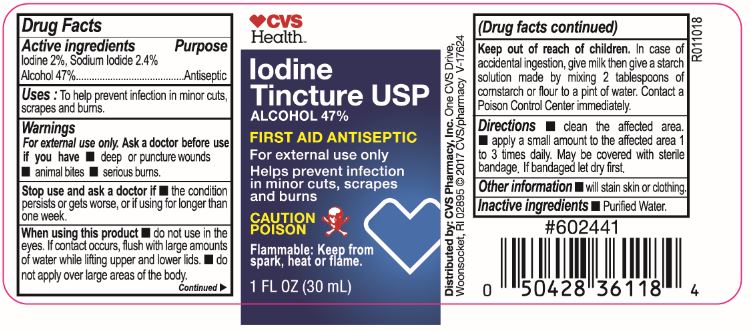 DRUG LABEL: CVS Iodine
NDC: 69842-213 | Form: LIQUID
Manufacturer: CVS Pharmacy
Category: otc | Type: HUMAN OTC DRUG LABEL
Date: 20231220

ACTIVE INGREDIENTS: IODINE 20 mg/1 mL; SODIUM IODIDE 20.4 mg/1 mL; ALCOHOL 470 mg/1 mL
INACTIVE INGREDIENTS: WATER

CVS Iodine Tincture USP

CVS Iodine Tincture USP

Drug Facts

Active Ingredient

Iodine 2%

Sodium Iodide 2.4%

Alcohol 47%

Purpose

Antiseptic

Indications

To help prevent infection in minor cuts, scrapes, and burns.

Warnings:

For external use only

Ask a doctor before use if you have

Deep or puncture wounds

Animal bites

Serious burns

Stop use and ask a doctor if

the condition persists or gets worse, if using this product for longer than 1 week.

Do not use

in the eyes. If contact occurs, flush with large amounts of water while lifting upper and lower lids.

Do not apply

over large areas of the body.

Keep out of reach of children.

- In case of accidental ingestion. Give milk, then give a starch solution made by mixing two tablespoofuls of cornstarch or flour to a pint of water. Contact a Poison Control Center immediately.

Directions

- Clean the affected area; apply a small amount on the area 1 to 3 times daily; may be covered with a sterile bandage. If bandaged, let dry first.

Inactive Ingredient

Purified water.

Other Information

Will stain skin and clothing

PRINCIPAL DISPLAY PANEL

CVS Health
Iodine Tincture USP
First Aid Antiseptic
1 FL OZ (30 mL)